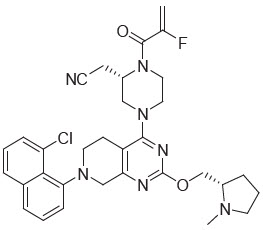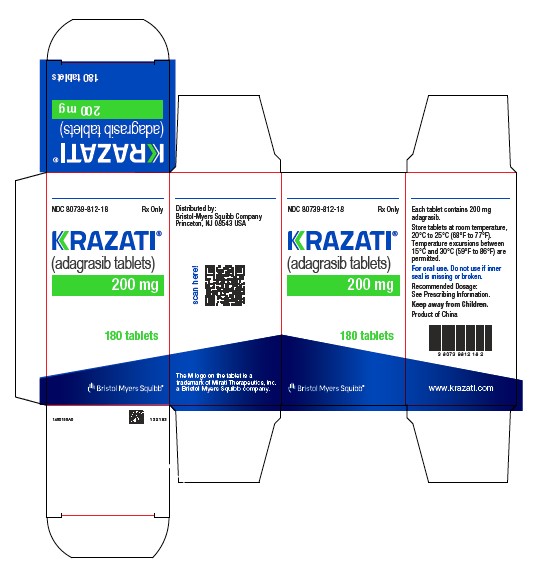 DRUG LABEL: KRAZATI
NDC: 80739-812 | Form: TABLET, COATED
Manufacturer: Mirati Therapeutics, Inc
Category: prescription | Type: HUMAN PRESCRIPTION DRUG LABEL
Date: 20260226

ACTIVE INGREDIENTS: ADAGRASIB 200 mg/1 1
INACTIVE INGREDIENTS: CROSPOVIDONE, UNSPECIFIED; HYPROMELLOSE 2910 (15 MPA.S); MAGNESIUM STEARATE; MALTODEXTRIN; MANNITOL; MEDIUM-CHAIN TRIGLYCERIDES; MICROCRYSTALLINE CELLULOSE; POLYDEXTROSE; SILICON DIOXIDE; TALC

HIGHLIGHTS OF PRESCRIBING INFORMATION

These highlights do not include all the information needed to use KRAZATI safely and effectively. See full prescribing information for KRAZATI.
KRAZATI® (adagrasib) tablets, for oral use
Initial U.S. Approval: 2022

RECENT MAJOR CHANGES

• Indications and Usage (1.1, 1.2) 06/2024

• Dosage and Administration (2.1, 2.2, 2.3) 06/2024

• Warnings and Precautions (5.1, 5.2, 5.3, 5.4) 06/2024

1 INDICATIONS AND USAGE

KRAZATI is an inhibitor of the RAS GTPase family indicated for:

Non-small cell lung cancer (NSCLC)*

- As a single agent, for the treatment of adult patients with KRAS G12C-mutated locally advanced or metastatic NSCLC, as determined by an FDA-approved test, who have received at least one prior systemic therapy. (1.1)

Colorectal cancer (CRC)*

- In combination with cetuximab, for the treatment of adult patients with KRAS G12C-mutated locally advanced or metastatic CRC, as determined by an FDA-approved test, who have received prior treatment with fluoropyrimidine-, oxaliplatin-, and irinotecan-based chemotherapy. (1.2)

*These indications are approved under accelerated approval based on objective response rate (ORR) and duration of response (DOR). Continued approval for these indications may be contingent upon verification and description of a clinical benefit in confirmatory trials. (1.1, 1.2)

2 DOSAGE AND ADMINISTRATION

- Recommended dosage as a single agent for NSCLC and in combination with cetuximab for CRC: 600 mg orally twice daily. (2.2)
- Swallow tablets whole with or without food. (2.2)

3 DOSAGE FORMS AND STRENGTHS

Tablets: 200 mg. (3)

4 CONTRAINDICATIONS

None. (4)

5 WARNINGS AND PRECAUTIONS

- Gastrointestinal Adverse Reactions: Monitor patients for diarrhea, nausea and vomiting and provide supportive care as needed. Withhold, reduce the dose or permanently discontinue based on severity. (2.3, 5.1)
- QTc Interval Prolongation: Avoid concomitant use of KRAZATI with other products with a known potential to prolong the QTc interval. Monitor ECG and electrolytes particularly potassium and magnesium, in patients at risk, and in patients taking medications known to prolong the QT interval. Correct electrolyte abnormalities. Withhold, reduce the dose, or permanently discontinue based on severity. (2.3, 5.2)
- Hepatotoxicity: Monitor liver laboratory tests prior to the start of KRAZATI and monthly for 3 months after and as clinically indicated. Reduce the dose, withhold, or permanently discontinue based on severity. (2.3, 5.3)
- Interstitial Lung Disease (ILD) / Pneumonitis: Monitor for new or worsening respiratory symptoms. Withhold KRAZATI for suspected ILD/pneumonitis and permanently discontinue if no other potential causes of ILD/pneumonitis are identified. (2.3, 5.4)

6 ADVERSE REACTIONS

- Single agent use in NCSLC: The most common adverse reactions (≥ 25%) were nausea, diarrhea, vomiting, fatigue, musculoskeletal pain, hepatotoxicity, renal impairment, edema, dyspnea, and decreased appetite. The most common (≥ 2%) Grade 3 or 4 laboratory abnormalities were decreased lymphocytes, decreased hemoglobin, increased alanine aminotransferase, increased aspartate aminotransferase, hypokalemia, hyponatremia, increased lipase, decreased leukocytes, decreased neutrophils and increased alkaline phosphatase. (6.1)
- In combination with cetuximab in CRC: The most common adverse reactions (≥ 25%) were rash, nausea, diarrhea, vomiting, fatigue, musculoskeletal pain, hepatotoxicity, headache, dry skin, abdominal pain, decreased appetite, edema, anemia, and cough. The most common (≥ 2%) Grade 3 or 4 laboratory abnormalities were decreased lymphocytes, decreased potassium, decreased magnesium, decreased hemoglobin, increased aspartate aminotransferase, increased lipase, decreased albumin, and increased alanine aminotransferase. (6.1)

To report SUSPECTED ADVERSE REACTIONS, contact Bristol-Myers Squibb at 1-800-721-5072 or FDA at 1-800-FDA-1088 or www.fda.gov/medwatch.

7 DRUG INTERACTIONS

See full prescribing information for clinically significant drug interactions with KRAZATI. (7)

- Strong CYP3A4 Inducers: Avoid concomitant use. (7.1)
- Strong CYP3A4 Inhibitors: Avoid concomitant use until adagrasib concentrations have reached steady state. (7.1)
- Sensitive CYP3A4 Substrates: Avoid concomitant use with sensitive CYP3A4 substrates. (7.2)
- Sensitive CYP2C9 or CYP2D6 Substrates or P-gp Substrates: Avoid concomitant use with sensitive CYP2C9 or CYP2D6 substrates or P-gp substrates where minimal concentration changes may lead to serious adverse reactions. (7.2)
- Drugs That Prolong QT Interval: Avoid concomitant use with KRAZATI. (7.3)

8 USE IN SPECIFIC POPULATIONS

Lactation: Advise not to breastfeed. (8.2)

FULL PRESCRIBING INFORMATION

1 INDICATIONS AND USAGE

1.1 KRAS G12C-Mutated Locally Advanced or Metastatic Non-Small Cell Lung Cancer

KRAZATI, as a single-agent, is indicated for the treatment of adult patients with KRAS G12C-mutated locally advanced or metastatic non-small cell lung cancer (NSCLC), as determined by an FDA-approved test [see Dosage and Administration (2.1)], who have received at least one prior systemic therapy.

This indication is approved under accelerated approval based on objective response rate (ORR) and duration of response (DOR) [see Clinical Studies (14.1)]. Continued approval for this indication may be contingent upon verification and description of a clinical benefit in a confirmatory trial.

1.2 KRAS G12C-Mutated Locally Advanced or Metastatic Colorectal Cancer

KRAZATI in combination with cetuximab is indicated for the treatment of adult patients with KRAS G12C-mutated locally advanced or metastatic colorectal cancer (CRC), as determined by an FDA-approved test [see Dosage and Administration (2.1)], who have received prior treatment with fluoropyrimidine-, oxaliplatin-, and irinotecan-based chemotherapy.

This indication is approved under accelerated approval based on ORR and DOR [see Clinical Studies (14.2)]. Continued approval for this indication may be contingent upon verification and description of a clinical benefit in a confirmatory trial.

2 DOSAGE AND ADMINISTRATION

2.1 Patient Selection

Non-Small Cell Lung Cancer

Select patients for treatment of locally advanced or metastatic NSCLC with KRAZATI based on the presence of KRAS G12C mutation in plasma or tumor specimens [see Clinical Studies (14.1)]. If no mutation is detected in a plasma specimen, test tumor tissue.

Colorectal Cancer

Select patients for treatment of locally advanced or metastatic CRC with KRAZATI based on the presence of KRAS G12C mutation in tumor specimens [see Clinical Studies (14.2)].

Information on FDA-approved tests for the detection of a KRAS G12C mutation is available at: https://www.fda.gov/CompanionDiagnostics

2.2 Recommended Dosage

The recommended dosage of KRAZATI as a single agent or in combination with cetuximab is 600 mg orally twice daily until disease progression or unacceptable toxicity.

Refer to the cetuximab prescribing information for cetuximab dosage information [see Clinical Studies (14.2)].

Take KRAZATI at the same time every day with or without food [see Clinical Pharmacology (12.3)]. Swallow tablets whole. Do not chew, crush or split tablets.

If vomiting occurs after taking KRAZATI, do not take an additional dose. Resume dosing at the next scheduled time.

If a dose is inadvertently missed, it should be skipped if greater than 4 hours have elapsed from the expected dosing time. Resume dosing at the next scheduled time.

2.3 Dosage Modifications for Adverse Reactions

Recommended dose reductions for adverse reactions for use of KRAZATI as a single agent or in combination with cetuximab are outlined in Table 1. If adverse reactions occur, a maximum of two dose reductions are permitted. Permanently discontinue KRAZATI in patients who are unable to tolerate 600 mg once daily.

Table 1: Recommended KRAZATI Dosage Reductions for Adverse Reactions
Dose Reduction | Dosage
First dose reduction | 400 mg twice daily
Second dose reduction | 600 mg once daily

Refer to the cetuximab prescribing information for dose modifications for adverse reactions associated with cetuximab.

When KRAZATI is administered in combination with cetuximab, withhold or permanently discontinue cetuximab when KRAZATI is withheld or permanently discontinued.

Treatment with KRAZATI as a single agent may be continued if cetuximab is permanently discontinued. [see Clinical Pharmacology (12.1), Clinical Studies (14.2)].

The recommended dosage modifications for adverse reactions are provided in Table 2.

Table 2: Recommended KRAZATI Dosage Modifications for Adverse Reactions
Adverse Reaction | Severity [Grading defined by National Cancer Institute Common Terminology Criteria for Adverse Events (NCI CTCAE) version 5.0.] | Dosage Modification [When KRAZATI is administered in combination with cetuximab, withhold or permanently discontinue treatment with cetuximab when withholding or permanently discontinuing treatment with KRAZATI.]
Nausea or vomiting despite appropriate supportive care (including anti-emetic therapy) [see Warnings and Precautions (5.1)] | Grade 3 or 4 | - Withhold KRAZATI until recovery to ≤ Grade 1 or return to baseline. - Resume KRAZATI at the next lower dose level.
Diarrhea despite appropriate supportive care (including anti-diarrheal therapy) [see Warnings and Precautions (5.1)] | Grade 3 or 4 | - Withhold KRAZATI until recovery to ≤ Grade 1 or return to baseline. - Resume KRAZATI at the next lower dose level.
QTc Interval Prolongation [see Warnings and Precautions (5.2)] | QTc absolute value greater than 500 ms or Greater than an increase of 60 ms from baseline | - Withhold KRAZATI until QTc interval less than 481 ms or return to baseline. - Resume KRAZATI at the next lower dose level.
 | Torsade de pointes, polymorphic ventricular tachycardia or signs or symptoms of serious or life-threatening arrhythmia | - Permanently discontinue KRAZATI
Hepatotoxicity [see Warnings and Precautions (5.3)] | Grade 2 AST or ALT | - Decrease KRAZATI to the next lower dose level.
Hepatotoxicity [see Warnings and Precautions (5.3)] | Grade 3 or 4 AST or ALT | - Withhold KRAZATI until recovery to ≤ Grade 1 or return to baseline. - Resume KRAZATI at the next lower dose level.
 | AST or ALT > 3 × ULN with total bilirubin > 2 × ULN in the absence of alternative causes | - Permanently discontinue KRAZATI
Interstitial Lung Disease / Pneumonitis [see Warnings and Precautions (5.4)] | Any Grade | - Withhold KRAZATI if ILD/pneumonitis is suspected. - Permanently discontinue KRAZATI if ILD/pneumonitis is confirmed
Other Adverse Reactions [see Adverse Reactions (6.1)] | Grade 3 or 4 | - Withhold KRAZATI until ≤ Grade 1 or return to baseline. - Resume KRAZATI at the next lower dose level.
ALT = alanine aminotransferase; AST = aspartate aminotransferase; ILD = Interstitial Lung Disease; ULN = upper limit of normal

3 DOSAGE FORMS AND STRENGTHS

Tablets: 200 mg, oval shaped, white to off-white, immediate release film coated tablets with "200" on one side and stylized "M" on the opposite side.

4 CONTRAINDICATIONS

None.

5 WARNINGS AND PRECAUTIONS

5.1 Gastrointestinal Adverse Reactions

KRAZATI can cause severe gastrointestinal adverse reactions.

In the pooled safety population [see Adverse Reactions (6.1)], who received single-agent KRAZATI, serious gastrointestinal adverse reactions observed were gastrointestinal bleeding in 3.8% including 0.8% Grade 3 or 4, gastrointestinal obstruction in 1.6% including 1.4% Grade 3 or 4, colitis in 0.5% including 0.3% Grade 3, ileus in 0.5%, and stenosis in 0.3%. In addition, nausea, diarrhea, or vomiting occurred in 89% of 366 patients, including 9% Grade 3. Nausea, diarrhea, or vomiting led to dosage interruption or dose reduction in 29% of patients and permanent discontinuation of adagrasib in 0.3%.

In patients who received KRAZATI in combination with cetuximab [see Adverse Reactions (6.1)], serious gastrointestinal adverse reactions included gastrointestinal bleeding in 8.5% including 1.1% Grade 3 or 4, gastrointestinal obstruction in 5.3% including 5.3% Grade 3 or 4, colitis in 1.1% including 1.1% Grade 3 and ileus in 1.1%. In addition, nausea, diarrhea, or vomiting occurred in 92% of 94 patients, including 6% Grade 3. Nausea, diarrhea, or vomiting led to adagrasib dose interruption or dose reduction in 23% of patients.

Monitor and manage patients using supportive care, including antidiarrheals, antiemetics, or fluid replacement, as indicated. Withhold, reduce the dose, or permanently discontinue KRAZATI based on severity [see Dosage and Administration (2.3)].

5.2 QTc Interval Prolongation

KRAZATI can cause QTc interval prolongation, which can increase the risk for ventricular tachyarrhythmias (e.g., torsades de pointes) or sudden death.

In the pooled safety population [see Adverse Reactions (6.1)] who received single-agent KRAZATI, 6% of 366 patients with at least one post-baseline electrocardiogram (ECG) assessment had an average QTc ≥ 501 msec and 11% of patients had an increase from baseline of QTc > 60 msec. KRAZATI causes concentration-dependent increases in the QTc interval [see Clinical Pharmacology (12.2)].

In patients who received KRAZATI in combination with cetuximab [see Adverse Reactions (6.1)], 5% of 93 patients with at least one post-baseline electrocardiogram (ECG) assessment had an average QTc ≥ 501 msec and 16% of patients had an increase from baseline of QTc > 60 msec.

Avoid concomitant use of KRAZATI with other products with a known potential to prolong the QTc interval [see Drug Interactions (7.3) and Clinical Pharmacology (12.2)]. Avoid use of KRAZATI in patients with congenital long QT syndrome and in patients with concurrent QTc prolongation.

Monitor ECGs and electrolytes, particularly potassium and magnesium, prior to starting KRAZATI, during concomitant use, and as clinically indicated in patients with congestive heart failure, bradyarrhythmias, electrolyte abnormalities, and in patients who are unable to avoid concomitant medications that are known to prolong the QT interval. Correct electrolyte abnormalities. Withhold, reduce the dose, or permanently discontinue KRAZATI depending on severity [see Dosage and Administration (2.3)].

5.3 Hepatotoxicity

KRAZATI can cause hepatotoxicity, which may lead to drug-induced liver injury and hepatitis.

In the pooled safety population of 366 patients [see Adverse Reactions (6.1)] who received single-agent KRAZATI, drug-induced liver injury was reported in 0.3% of patients, including 0.3% Grade 3. A total of 32% of patients who received adagrasib had increased alanine aminotransferase (ALT)/increased aspartate aminotransferase (AST); 5% were Grade 3 and 0.5% were Grade 4. The median time to first onset of increased ALT/AST was 3 weeks (range: 0.1 to 48). Overall hepatotoxicity occurred in 37%, and 7% were Grade 3 or 4. Hepatotoxicity leading to dose interruption or reduction occurred in 12% of patients. Adagrasib was discontinued due to hepatotoxicity in 0.5% of patients.

In patients who received KRAZATI in combination with cetuximab [see Adverse Reactions (6.1)], 29% had increased alanine aminotransferase (ALT)/increased aspartate aminotransferase (AST); 5% were Grade 3 and 1.1% were Grade 4. The median time to first onset of increased ALT/AST was 4 weeks (range: 0.1 to 27). Overall hepatotoxicity occurred in 38%, and 10% were Grade 3 or 4. Hepatotoxicity leading to adagrasib dose interruption or reduction occurred in 12% of patients.

Monitor liver laboratory tests (AST, ALT, alkaline phosphatase and total bilirubin) prior to the start of KRAZATI and monthly for 3 months or as clinically indicated, with more frequent testing in patients who develop transaminase elevations. Reduce the dose, withhold, or permanently discontinue KRAZATI based on severity [see Dosage and Administration (2.3) and Adverse Reactions (6.1)].

5.4 Interstitial Lung Disease / Pneumonitis

KRAZATI can cause interstitial lung disease (ILD)/pneumonitis, which can be fatal.

In the pooled safety population [see Adverse Reactions (6.1)] who received single-agent KRAZATI, ILD/pneumonitis occurred in 4.1% of patients, 1.4% were Grade 3 or 4, and one case was fatal. The median time to first onset for ILD/pneumonitis was 12 weeks (range: 5 to 31 weeks). Adagrasib was discontinued due to ILD/pneumonitis in 0.8% of patients.

In patients who received KRAZATI in combination with cetuximab [see Adverse Reactions (6.1)], Grade 1 ILD/pneumonitis occurred in 1.1% of patients. The time to first onset for ILD/pneumonitis was 38 weeks.

Monitor patients for new or worsening respiratory symptoms indicative of ILD/pneumonitis (e.g., dyspnea, cough, fever) during treatment with KRAZATI. Withhold KRAZATI in patients with suspected ILD/pneumonitis and permanently discontinue KRAZATI if no other potential causes of ILD/pneumonitis are identified [see Dosage and Administration (2.3)].

6 ADVERSE REACTIONS

The following clinically significant adverse reactions are described elsewhere in the labeling:

- Gastrointestinal Adverse Reactions [see Warnings and Precautions (5.1)]
- QTc Interval Prolongation [see Warnings and Precautions (5.2)]
- Hepatotoxicity [see Warnings and Precautions (5.3)]
- Interstitial Lung Disease (ILD)/Pneumonitis [see Warnings and Precautions (5.4)]

6.1 Clinical Trials Experience

Because clinical trials are conducted under widely varying conditions, adverse reaction rates observed in the clinical trials of a drug cannot be directly compared to rates in the clinical trials of another drug and may not reflect the rates observed in practice.

The pooled safety population described in the WARNINGS AND PRECAUTIONS reflect exposure to adagrasib as a single agent at 600 mg orally twice daily in 366 patients with NSCLC and other solid tumors enrolled in KRYSTAL-1 and KRYSTAL-12 (NCT04685135), respectively. Among 366 patients who received adagrasib, 39% of patients were exposed for 6 months or longer and 12% were exposed for greater than one year. In this pooled safety population, the most common (≥ 25%) adverse reactions were nausea (70%), diarrhea (69%), vomiting (57%), fatigue (55%), musculoskeletal pain (38%), hepatotoxicity (37%), renal impairment (33%), edema (30%), dyspnea (26%), and decreased appetite (29%). In this pooled safety population, the most common Grade 3 or 4 (≥ 2%) laboratory abnormalities were decreased lymphocytes (20%), decreased hemoglobin (7%), increased alanine aminotransferase (4.5%), increased aspartate aminotransferase (4.2%), hypokalemia (3.6%), hyponatremia (3.4%), increased lipase (2.5%), decreased leukocytes (2.5%), decreased neutrophils (2.3%), and increased alkaline phosphatase (2.0%).

The data described in WARNINGS AND PRECAUTIONS and below also reflects exposure to adagrasib in combination with cetuximab in 94 patients with KRAS G12C-mutated, locally advanced or metastatic CRC in KRYSTAL-1.

Non-Small Cell Lung Cancer

The safety of adagrasib was evaluated in patients with KRAS G12C-mutated, locally advanced or metastatic NSCLC in KRYSTAL-1 [see Clinical Studies (14.1)]. Patients received adagrasib 600 mg orally twice daily (n = 116). Among patients who received adagrasib, 45% were exposed for 6 months or longer and 4% were exposed for greater than one year.

The median age of patients who received adagrasib was 64 years (range 25 to 89), 56% female, 84% White, 8% Black or African American, and 4.3% Asian.

Serious adverse reactions occurred in 57% of patients who received adagrasib. Serious adverse reactions in ≥ 2% of patients were pneumonia (17%), dyspnea (9%), renal impairment (8%), sepsis (5%), hypoxia (4.3%), pleural effusion (4.3%), respiratory failure (4.3%), anemia (3.4%), cardiac failure (3.4%), hyponatremia (3.4%), hypotension (3.4%), muscular weakness (3.4%), pyrexia (3.4%), dehydration (2.6%), diarrhea (2.6%), mental status changes (2.6%), pulmonary embolism (2.6%), and pulmonary hemorrhage (2.6%). Fatal adverse reactions occurred in 11% of patients who received adagrasib due to pneumonia (3.4%), respiratory failure (1.7%), sudden death (1.7%), cardiac failure (0.9%), cerebrovascular accident (0.9%), mental status change (0.9%), pulmonary embolism (0.9%), and pulmonary hemorrhage (0.9%).

Permanent discontinuation of adagrasib due to an adverse reaction occurred in 13% of patients. Adverse reactions which resulted in permanent discontinuation of adagrasib occurring in two patients each (1.7%) were pneumonia and pneumonitis and occurring in one patient each (0.9%) were cerebrovascular accident, dyspnea, decreased ejection fraction, encephalitis, gastrointestinal obstruction, hemorrhage, hepatotoxicity, hypotension, muscular weakness, pulmonary embolism, pyrexia, respiratory failure and sepsis.

Dose interruptions of adagrasib due to an adverse reaction occurred in 77% of patients. Adverse reactions requiring dosage interruption in ≥ 2% of patients who received adagrasib included nausea, hepatotoxicity, fatigue, vomiting, pneumonia, renal impairment, diarrhea, QTc interval prolongation, anemia, dyspnea, increased lipase, decreased appetite, dizziness, hyponatremia, muscular weakness, increased amylase, pneumonitis, sepsis and decreased weight.

Dose reductions of adagrasib due to an adverse reaction occurred in 28% of patients. Adverse reactions which required dose reductions in ≥ 2% of patients who received adagrasib included hepatotoxicity, fatigue, nausea, diarrhea, vomiting, and renal impairment.

The most common adverse reactions (≥ 20%) were diarrhea, nausea, fatigue, vomiting, musculoskeletal pain, hepatotoxicity, renal impairment, dyspnea, edema, decreased appetite, cough, pneumonia, dizziness, constipation, abdominal pain, and QTc interval prolongation. The most common laboratory abnormalities (≥ 25%) were decreased lymphocytes, increased aspartate aminotransferase, decreased sodium, decreased hemoglobin, increased creatinine, decreased albumin, increased alanine aminotransferase, increased lipase, decreased platelets, decreased magnesium, and decreased potassium.

Table 3 summarizes the adverse reactions in KRYSTAL-1.

Table 3: Adverse Reactions (≥ 20%) in Patients with KRAS G12C-mutated NSCLC Who Received Adagrasib in KRYSTAL-1
Adverse Reaction | Adagrasib N = 116
 | All Grades (%) | Grade 3 or 4 (%)
Gastrointestinal Disorders
Diarrhea [Grouped term.] | 70 | 0.9
Nausea | 69 | 4.3
Vomiting | 56 | 0.9
Constipation | 22 | 0
Abdominal pain | 21 | 0
General Disorders and Administration Site Conditions
Fatigue | 59 | 7
Edema | 32 | 0
Musculoskeletal and Connective Tissue Disorders
Musculoskeletal pain | 41 | 7
Hepatobiliary Disorders
Hepatotoxicity, [Hepatotoxicity includes mixed liver injury, blood alkaline phosphatase increased, alanine aminotransferase increased, aspartate aminotransferase increased, liver function test increased, blood bilirubin increased, and bilirubin conjugated increased.] | 37 | 10
Renal and Urinary Disorders
Renal impairment, [Renal impairment includes acute kidney injury and increased blood creatinine.] | 36 | 6
Respiratory
Dyspnea | 35 | 10
Cough | 24 | 0.9
Metabolism and Nutrition Disorders
Decreased appetite | 30 | 4.3
Infections and Infestations
Pneumonia | 24 | 17
Nervous System Disorders
Dizziness | 23 | 0.9
Cardiac Disorders
Electrocardiogram QT prolonged | 20 | 6

Table 4 summarizes the laboratory abnormalities in KRYSTAL-1.

Table 4: Select Laboratory Abnormalities Occurring (≥ 25%) That Worsened from Baseline in Patients with KRAS G12C-mutated NSCLC Who Received Adagrasib in KRYSTAL-1
Laboratory Abnormality | Adagrasib [Denominator used to calculate the rate varied from 106 to 113 based on the number of patients with a baseline value and at least one post-treatment value.]
Laboratory Abnormality | All Grades (%) | Grade 3 or 4 (%)
Hematology
Lymphocytes decreased | 64 | 25
Hemoglobin decreased | 51 | 8
Platelets decreased | 27 | 0
Chemistry
Aspartate aminotransferase increased | 52 | 6
Sodium decreased | 52 | 8
Creatinine increased | 50 | 0
Albumin decreased | 50 | 0.9
Alanine aminotransferase increased | 46 | 5
Lipase increased | 35 | 1.8
Magnesium decreased | 26 | 0
Potassium decreased | 26 | 3.5

Colorectal Cancer

The safety of adagrasib combined with cetuximab was evaluated in 94 patients with KRAS G12C-mutated, locally advanced or metastatic CRC in KRYSTAL-1 [see Clinical Studies (14.2)]. Patients started treatment with adagrasib 600 mg twice daily in combination with cetuximab weekly (n = 17) or every two weeks (n = 77). Among patients who received adagrasib in combination with cetuximab, 60% were exposed for greater than 6 months and 12% were exposed for greater than 12 months.

Serious adverse reactions occurred in 30% of patients who received adagrasib in combination with cetuximab. The most common serious adverse reactions (≥ 2%) were pneumonia (4.3%), pleural effusion, pyrexia, acute kidney injury, dehydration, and small intestinal obstruction (2.1% each).

A fatal adverse reaction of pneumonia occurred in 1 patient who received adagrasib in combination with cetuximab.

Adverse reactions leading to discontinuation of adagrasib occurred in 2 patients. Adverse reactions which resulted in permanent discontinuation of adagrasib (1 patient each) included abdominal pain and prolonged QT interval.

Adverse reactions leading to dose interruptions of adagrasib occurred in 62% of patients. The most common adverse reactions or laboratory abnormalities leading to dose interruption in ≥ 2% of patients who received adagrasib included diarrhea, nausea, vomiting, abdominal pain, dizziness, headache, pneumonia, alanine aminotransferase increased, aspartate aminotransferase increased, dyspnea, fatigue, pleural effusion, rash, anemia, electrocardiogram QT prolongation, blood bilirubin increased, blood creatinine increased, decreased appetite, dehydration, hemorrhage, hypomagnesemia, lipase increased, muscular weakness, musculoskeletal pain, and pyrexia.

Adverse reactions leading to dose reductions of adagrasib occurred in 35% of patients. The most common adverse reactions or laboratory abnormalities leading to dose reductions in ≥ 2% of patients who received adagrasib included fatigue, increased aspartate aminotransferase, increased alanine aminotransferase, nausea, decreased appetite, electrocardiogram QT prolongation, dizziness, acute kidney injury, diarrhea, dysarthria, and vomiting.

The most common adverse reactions (≥ 20%) were rash, nausea, diarrhea, vomiting, fatigue, musculoskeletal pain, hepatotoxicity, headache, dry skin, abdominal pain, decreased appetite, edema, anemia, dizziness, cough, constipation, and peripheral neuropathy.

The most common laboratory abnormalities (≥ 25%) were decreased lymphocytes, decreased hemoglobin, decreased leukocytes, increased alanine aminotransferase, decreased magnesium, decreased albumin, increased lipase, decreased potassium, increased aspartate aminotransferase, increased creatinine, decreased sodium, decreased calcium, increased amylase, and increased alkaline phosphatase.

Table 5 summarizes the adverse reactions in patients with metastatic CRC in KRYSTAL-1.

Table 5: Adverse Reactions (≥ 20 %) in Patients with KRAS G12C-mutated CRC Received Adagrasib in Combination with Cetuximab in KRYSTAL-1
Adverse Reaction [Graded per CTCAE version 5.0.] | Adagrasib in Combination with Cetuximab N = 94
 | All Grades (%) | Grade 3 or 4 (%)
Skin and subcutaneous tissue disorders
Rash [Grouped term; includes multiple related terms.] | 84 | 4.3
Dry skin | 36 | 0
Gastrointestinal Disorders
Nausea | 68 | 2.1
Diarrhea | 65 | 5
Vomiting | 57 | 0
Abdominal pain | 30 | 4.3
Constipation | 23 | 0
General Disorders and Administration Site Conditions
Fatigue | 57 | 3.2
Musculoskeletal pain | 47 | 4.3
Edema | 28 | 0
Hepatobiliary Disorders
Hepatotoxicity | 38 | 10
Nervous System Disorders
Headache | 37 | 4.3
Dizziness | 24 | 2.1
Peripheral neuropathy | 20 | 1.1
Metabolism and Nutrition Disorders
Decreased appetite | 30 | 0
Blood and lymphatic system disorders
Anemia | 27 | 7
Respiratory
Cough | 25 | 0

Other clinically relevant adverse reactions observed in less than 20% of patients were infusion related reactions (15%).

Table 6 summarizes the laboratory abnormalities in patients with metastatic CRC in KRYSTAL-1.

Table 6: Selected Laboratory Abnormalities (≥ 25%) in Patients Who Received Adagrasib in Combination with Cetuximab in KRYSTAL-1
Laboratory Abnormality | Adagrasib in Combination with Cetuximab [The denominator used to calculate the rate varied from 82 to 92 based on the number of patients with a baseline value and at least one post-treatment value.]
Laboratory Abnormality | All Grades (%) | Grade 3 or 4 (%)
Hematology
Lymphocytes decreased | 63 | 17
Hemoglobin decreased | 48 | 5
Leukocytes decreased | 27 | 1.1
Chemistry
Alanine aminotransferase increased | 51 | 2.2
Magnesium decreased | 49 | 7
Albumin decreased | 46 | 2.2
Lipase increased | 41 | 3.3
Potassium decreased | 40 | 9
Aspartate aminotransferase increased | 39 | 4.3
Creatinine increased | 30 | 1.1
Sodium decreased | 30 | 0
Calcium decreased | 29 | 1.1
Amylase increased | 29 | 0
Alkaline phosphatase increased | 29 | 1.1

7 DRUG INTERACTIONS

7.1 Effects of Other Drugs on KRAZATI

Strong CYP3A4 Inducers

Avoid concomitant use of KRAZATI with strong CYP3A inducers.

Adagrasib is a CYP3A4 substrate. Concomitant use of KRAZATI with a strong CYP3A inducer reduces adagrasib exposure [see Clinical Pharmacology (12.3)], which may reduce the effectiveness of KRAZATI.

Strong CYP3A4 Inhibitors

Avoid concomitant use of KRAZATI with strong CYP3A inhibitors until adagrasib concentrations have reached steady state (after approximately 8 days).

Adagrasib is a CYP3A4 substrate. If adagrasib concentrations have not reached steady state, concomitant use of a strong CYP3A inhibitor will increase adagrasib concentrations, [see Clinical Pharmacology (12.3)], which may increase the risk of KRAZATI adverse reactions.

7.2 Effects of KRAZATI on Other Drugs

Sensitive CYP3A Substrates

Avoid concomitant use of KRAZATI with sensitive CYP3A substrates unless otherwise recommended in the Prescribing Information for these substrates.

Adagrasib is a CYP3A inhibitor. Concomitant use with KRAZATI increases exposure of CYP3A substrates [see Clinical Pharmacology (12.3)], which may increase the risk of adverse reactions related to these substrates.

Sensitive CYP2C9 Substrates

Avoid concomitant use of KRAZATI with sensitive CYP2C9 substrates where minimal concentration changes may lead to serious adverse reactions unless otherwise recommended in the Prescribing Information for these substrates.

Adagrasib is a CYP2C9 inhibitor. Concomitant use with KRAZATI increases exposure of CYP2C9 substrates [see Clinical Pharmacology (12.3)], which may increase the risk of adverse reactions related to these substrates.

Sensitive CYP2D6 Substrates

Avoid concomitant use of KRAZATI with sensitive CYP2D6 substrates where minimal concentration changes may lead to serious adverse reactions unless otherwise recommended in the Prescribing Information for these substrates.

Adagrasib is a CYP2D6 inhibitor. Concomitant use with KRAZATI increases exposure of CYP2D6 substrates [see Clinical Pharmacology (12.3)], which may increase the risk of adverse reactions related to these substrates.

P-gp Substrates

Avoid concomitant use of KRAZATI with P-gp substrates where minimal concentration changes may lead to serious adverse reactions unless otherwise recommended in the Prescribing Information for these substrates.

Adagrasib is a P-gp inhibitor. Concomitant use with KRAZATI increases exposure of P-gp substrates [see Clinical Pharmacology (12.3)], which may increase the risk of adverse reactions related to these substrates.

7.3 Drugs That Prolong QTc Interval

Avoid concomitant use of KRAZATI with other product(s) with a known potential to prolong the QTc interval. If concomitant use cannot be avoided, monitor electrocardiogram and electrolytes prior to starting KRAZATI, during concomitant use, and as clinically indicated [see Warnings and Precautions (5.2)]. Withhold KRAZATI if the QTc interval is > 500 ms or the change from baseline is > 60 ms [see Dosage and Administration (2.3)].

Adagrasib causes QTc interval prolongation [see Clinical Pharmacology (12.2)]. Concomitant use of KRAZATI with other products that prolong the QTc interval may result in a greater increase in the QTc interval and adverse reactions associated with QTc interval prolongation, including Torsade de pointes, other serious arrythmias, and sudden death [see Warnings and Precautions (5.2)].

8 USE IN SPECIFIC POPULATIONS

8.1 Pregnancy

Risk Summary

There are no available data on the use of KRAZATI in pregnant women. In animal reproduction studies, oral administration of adagrasib to pregnant rats and rabbits during the period of organogenesis did not cause adverse development effects or embryo-fetal lethality at exposures below the human exposure at the recommended dose of 600 mg twice daily (see Data).

In the U.S. general population, the estimated background risk of major birth defects and miscarriage in clinically recognized pregnancies is 2% to 4% and 15% to 20%, respectively.

Data

Animal Data

In a rat embryo-fetal development study, once daily oral administration of adagrasib to pregnant rats during the period of organogenesis resulted in maternal toxicity (reduced body weight and food intake, and adverse clinical signs leading to moribund condition and early termination) and lower fetal body weight at 270 mg/kg dose level (approximately 2 times the recommended dose of 600 mg twice daily based on body surface area [BSA]). Adagrasib induced skeletal malformations, such as bent limbs, and skeletal variations, such as bent scapula, wavy ribs, and supernumerary short cervical ribs at 270 mg/kg, which were secondary to maternal toxicity and reduced fetal body weight.

In a rabbit embryo-fetal development study, once daily oral administration of adagrasib during the period of organogenesis resulted in lower fetal body weight and increased litter frequency of unossified sternebra at 30 mg/kg (approximately 0.11 times the human exposure based on area under the curve [AUC] at the clinical dose of 600 mg twice daily). This skeletal variation was associated with maternal toxicities, including reduced mean body weight and decreased food consumption. Adagrasib exposure did not cause adverse developmental effects and did not affect embryo-fetal survival in rabbits at doses up to 30 mg/kg once daily.

8.2 Lactation

Risk Summary

There are no data on the presence of adagrasib or its metabolites in human milk, the effects on the breastfed child, or on milk production. Because of the potential for serious adverse reactions in breastfed children, advise women not to breastfeed during treatment with KRAZATI and for 1 week after the last dose.

8.3 Females and Males of Reproductive Potential

Infertility

Based on findings from animal studies, KRAZATI may impair fertility in females and males of reproductive potential [see Nonclinical Toxicology (13.1)].

8.4 Pediatric Use

The safety and effectiveness of KRAZATI has not been established in pediatric patients.

8.5 Geriatric Use

Of 116 patients with metastatic NSCLC who received adagrasib 600 mg orally twice daily in KRYSTAL-1, 49% (57 patients) were ≥ 65 years of age and 13% (15 patients) were ≥ 75 years of age. No overall differences in safety or effectiveness were observed between older and younger patients.

Of 94 patients with metastatic CRC who received adagrasib 600 mg orally twice daily in combination with cetuximab in KRISTAL-1, 33% (31 patients) were ≥ 65 years of age and 2.1% (2 patients) were ≥ 75 years of age. No overall differences in safety or effectiveness were observed between older and younger patients.

11 DESCRIPTION

Adagrasib is an irreversible inhibitor of KRAS G12C and belongs to the RAS GTPase family. The molecular formula is C32H35ClFN7O2 and the molecular weight is 604.1 g/mol. The chemical name is {(2S)-4-[7-(8-chloronaphthalen-1-yl)-2-{[(2S)-1-methylpyrrolidin-2-yl]- methoxy}-5,6,7,8-tetrahydropyrido[3,4-d]pyrimidin-4-yl]-1-(2-fluoroprop-2-enoyl)piperazin-2-yl}acetonitrile. Adagrasib has the following chemical structure:

Adagrasib is a crystalline solid. The solubility of adagrasib in the aqueous media decreases over the range pH 1.2 to 7.4 from > 262 mg/mL to < 0.010 mg/mL.

KRAZATI (adagrasib) tablets for oral administration contain 200 mg of adagrasib. The following are inactive ingredients: colloidal silicon dioxide, crospovidone, magnesium stearate (vegetable sourced), mannitol, and microcrystalline cellulose. The tablet film coating contains hypromellose, maltodextrin, medium chain triglycerides (vegetable sourced), polydextrose, talc, and titanium dioxide.

12 CLINICAL PHARMACOLOGY

12.1 Mechanism of Action

Adagrasib is an irreversible inhibitor of KRAS G12C that covalently binds to the mutant cysteine in KRAS G12C and locks the mutant KRAS protein in its inactive state that prevents downstream signaling without affecting wild-type KRAS protein. Adagrasib inhibited tumor cell growth and viability in cells harboring KRAS G12C mutations and resulted in tumor regression in KRAS G12C-mutated tumor xenograft models with minimal off-target activity. Adagrasib in combination with cetuximab had increased antitumor activity in some cell line-derived and patient-derived KRAS G12C-mutant CRC tumor xenograft models compared to adagrasib or cetuximab alone.

12.2 Pharmacodynamics

Adagrasib exposure-response relationships and the time course of pharmacodynamic response are unknown.

Cardiac Electrophysiology

Adagrasib increased QTc in a concentration-dependent manner. Based on the concentration-QTcF relationship, the mean (90% CI) QTcF change from baseline (ΔQTcF) was 18 (15, 21) ms at the mean steady-state maximum concentration (Cmax,ss) in patients after administration of adagrasib 600 mg twice daily [see Warnings and Precautions (5.2)].

12.3 Pharmacokinetics

The pharmacokinetics of adagrasib were studied in healthy subjects and in patients with KRAS G12C-mutated NSCLC or CRC. Adagrasib pharmacokinetic data are presented as mean (percent coefficient of variation) unless otherwise specified.

Adagrasib AUC and Cmax increase dose proportionally over the dose range of 400 mg to 600 mg (0.67 to 1 times the approved recommended dose). Adagrasib steady-state was reached within 8 days following administration of the approved recommended dosage and accumulation was approximately 6-fold.

Absorption

The median (min, max) Tmax of adagrasib is approximately 6 (6, 12) hours.

Effect of Food

No clinically significant differences in the pharmacokinetics of adagrasib were observed following administration of a high-fat and high-calorie meal (containing approximately 900 to 1000 calories, 50% from fat).

Distribution

The apparent volume of distribution of adagrasib is 942 L (57%). Human plasma protein binding of adagrasib is approximately 98% in vitro.

Elimination

The adagrasib terminal elimination half-life is 23 hours (16%) and the apparent oral clearance (CL/F) is 37 L/h (54%) in patients.

Metabolism

Adagrasib is metabolized primarily by CYP3A4 following single dose administration. Adagrasib inhibits its own CYP3A4 metabolism following multiple dosing to steady-state which permits CYP2C8, CYP1A2, CYP2B6, CYP2C9, and CYP2D6 to contribute to its metabolism at steady-state.

Excretion

Following a single oral dose of radiolabeled adagrasib, approximately 75% of the dose was recovered in feces (14% as unchanged) and 4.5% recovered in urine (2% as unchanged).

Specific Populations

No clinically significant differences in the pharmacokinetics of adagrasib based on age (19 to 89 years), sex, race (White, Black or African American, or Asian), body weight (36 to 146 kg), ECOG PS (0, 1), tumor type (NSCLC or CRC), or tumor burden. No clinically significant differences in the pharmacokinetics of adagrasib are expected in patients with mild to severe renal impairment (CLcr 15 to < 90 mL/min estimated by Cockcroft-Gault equation) or in patients with mild to severe hepatic impairment (Child-Pugh classes A to C).

Drug Interaction Studies

Clinical Studies and Model-Informed Approaches

The following table describes the effect of other drugs on the pharmacokinetics of adagrasib.

Table 7: Effect of Other Drugs on Adagrasib
Concomitant Drug | Adagrasib Dosage | Changes in Cmax or AUC of Adagrasib
Concomitant Drug | Adagrasib Dosage | Cmax % Decrease | AUC % Decrease
Rifampin (a strong CYP3A inducer) | 600 mg single dose | 88% | 95%
Rifampin (a strong CYP3A inducer) | 600 mg multiple doses | > 61% [Predicted changes in Cmax or AUC of adagrasib.] | > 66%
Cmax = maximum plasma concentration; AUC = area under the plasma concentration-time curve

Strong CYP3A Inhibitors: Adagrasib Cmax increased by 2.4-fold and AUC increased by 4-fold following concomitant use of a single dose of 200 mg (0.33 times the approved recommended dose) with itraconazole (a strong CYP3A inhibitor). No clinically significant differences in the pharmacokinetics of adagrasib at steady state were predicted when used concomitantly with itraconazole.

No clinically significant differences in the pharmacokinetics of adagrasib were predicted or observed when used concomitantly with efavirenz (a moderate CYP3A inducer), pantoprazole (a proton pump inhibitor), or rosuvastatin (a BCRP/OATP substrate).

The following table describes the effect of adagrasib on the pharmacokinetics of other drugs.

Table 8: Effect of Adagrasib on Other Drugs
Concomitant Drug | Adagrasib Dosage | Fold Increase of Concomitant Drug
Concomitant Drug | Adagrasib Dosage | Cmax | AUC
Midazolam (a sensitive CYP3A substrate) | 400 mg [0.66 times the approved recommended dosage.] twice daily | 4.8-fold | 21-fold
Midazolam (a sensitive CYP3A substrate) | 600 mg twice daily | 3.1-fold [Predicted changes in Cmax or AUC of concomitant drug.] | 31-fold
Warfarin (a sensitive CYP2C9 substrate) | 600 mg twice daily | 1.1-fold | 2.9-fold
Dextromethorphan (a sensitive CYP2D6 substrate) | 400 mg twice daily | 1.9-fold | 1.8-fold
Dextromethorphan (a sensitive CYP2D6 substrate) | 600 mg twice daily | 1.7-fold | 2.4-fold
Digoxin (a P-gp substrate) | 600 mg twice daily | 1.9-fold | 1.5-fold
Cmax = maximum plasma concentration; AUC = area under the plasma concentration-time curve

In Vitro Studies

Cytochrome P450 (CYP) Enzymes: Adagrasib may inhibit CYP2B6.

Transporter Systems: Adagrasib may be a substrate of BCRP and may inhibit MATE-1/MATE-2K.

13 NONCLINICAL TOXICOLOGY

13.1 Carcinogenesis, Mutagenesis, Impairment of Fertility

Carcinogenicity studies have not been conducted with adagrasib.

Adagrasib was not mutagenic in an in vitro bacterial reverse mutation (Ames) assay and was not genotoxic in an in vitro chromosomal aberration assay or an in vivo micronucleus assay in rats.

Fertility studies were not conducted with adagrasib. In toxicology studies of up to 13-weeks in duration in rats, oral administration of adagrasib induced phospholipidosis which increased vacuolation in female reproductive organs, including vacuolation in ovaries (corpora lutea, macrophage or interstitial cells) and uterus (glandular epithelium), and atrophy with mucification of the vaginal mucosa at doses ≥ 150 mg/kg (approximately equal to or greater than the human exposure at the recommended dose based on area under the curve [AUC]). These findings reversed after cessation of dosing in the 28-day study but in the 13-week study, pigmented macrophage aggregates were observed in the ovaries of female rats after the recovery period. In a 28-day repeat-dose toxicology study, oral administration of adagrasib to male rats induced atrophy and epithelial vacuolation of the prostate gland and seminal vesicles at 300 mg/kg (approximately 1.6 times the human exposure at the recommended dose based on AUC). These findings resolved after cessation of treatment.

13.2 Animal Toxicology and/or Pharmacology

Phospholipidosis (vacuolation and/or presence of foamy macrophages) was observed in multiple organs (e.g., lung, trachea, heart, skeletal, ovaries, uterus, adrenal gland, kidney, liver, lymph nodes, spleen, thymus, and thyroid in rats; and heart and lung in dogs) after repeated oral administration of adagrasib in rats and dogs. In toxicology studies of up to 13-week duration in rats, phospholipidosis was observed at doses ≥ 150 mg/kg (approximately ≥ 2 times the human exposure at the recommended dose based on AUC). In a dog 28-day toxicity study, this effect was observed at 25 mg/kg (approximately equal to the human exposure at the recommended dose based on AUC). The extent of vacuolization and the presence of foamy macrophages were more prominent in the rat compared to dogs, and evidence of reversibility after cessation of treatment was noted for most organs. The significance of this finding in humans in unknown.

14 CLINICAL STUDIES

14.1 Non-Small Cell Lung Cancer

The efficacy of adagrasib was evaluated in KRYSTAL-1 (NCT03785249), a multicenter, single-arm, open-label expansion cohort study. Eligible patients were required to have locally advanced or metastatic KRAS G12C-mutated NSCLC who previously received treatment with a platinum-based regimen and an immune checkpoint inhibitor, an Eastern Cooperative Oncology Group Performance Status (ECOG PS) of 0 or 1, and at least one measurable lesion as defined by Response Evaluation criteria in Solid Tumors (RECIST v1.1). Identification of a KRAS G12C mutation was prospectively determined by local testing using tissue specimens. Patients received adagrasib 600 mg orally twice daily until unacceptable toxicity or disease progression. Tumor assessments were performed every 6 weeks. The major efficacy outcome measures were confirmed objective response rate (ORR) and duration of response (DOR) as evaluated by blinded independent central review (BICR) according to RECIST v1.1.

In the efficacy population, KRAS G12C mutation status was determined by prospective local testing using tumor tissue specimens. Of the 112 patients with KRAS G12C mutation, tissue samples from 88% (98/112) patients were tested retrospectively using the QIAGEN therascreen KRAS RGQ PCR Kit. While 89% (87/98) of patients were positive for KRAS G12C mutation, 11% (11/98) did not have a KRAS G12C mutation identified. In addition, plasma samples from 63% (71/112) patients were tested retrospectively using Agilent Resolution ctDx FIRST assay. While 66% (47/71) of patients were positive for KRAS G12C mutation, 34% (24/71) did not have a KRAS G12C mutation identified.

A total of 112 patients had at least one measurable lesion at baseline as assessed by BICR according to RECIST v1.1.

The baseline demographic and disease characteristics in the efficacy population were: median age 64 years (range: 25 to 89), 55% female, 83% White, 8% were Black or African American, 4% Asian, 4% race not reported, 0.9% American Indian or Alaska Native, 16% Eastern Cooperative Oncology Group (ECOG) performance status (PS) 0 and 83% ECOG PS 1. Tumor histology was 97% adenocarcinoma and 89% of patients had metastatic disease. Patients received a median of 2 prior systemic therapies (range 1 to 7); 43% received 1 prior line, 35% received 2 prior lines, 10% received 3 prior lines and 12% received 4 or more prior lines, 98% received both prior platinum and prior anti-PD-1/PD-L1 therapy. Sites of extra-thoracic disease included bone 42%, brain 30%, adrenals 21%, and liver 21%.

Efficacy results are summarized in Table 9.

Table 9: Efficacy Results for KRYSTAL-1
Efficacy Parameter | Adagrasib (n = 112)
Objective Response Rate (95% CI) [Assessed by BICR.] | 43 (34, 53)
Complete response rate, % | 0.9
Partial response rate, % | 42
Duration of Response
Median [Estimate using Kaplan-Meier method.] in months (95% CI) | 8.5 (6.2, 13.8)
Patients with duration ≥ 6 months [Observed proportion of patients with duration of response beyond landmark time.] , % | 58
CI = Confidence Interval

14.2 Colorectal Cancer

The efficacy of adagrasib in combination with cetuximab was evaluated in KRYSTAL-1, a multicenter, single-arm, open-label expansion cohort study. Eligible patients were required to have locally advanced or metastatic KRAS G12C-mutated CRC and to have previously received therapy with fluoropyrimidine-, oxaliplatin-, and irinotecan-based chemotherapy, a VEGF inhibitor if eligible, and an ECOG PS of 0 or 1.

Patients initiated treatment with adagrasib 600 mg orally twice daily in combination with cetuximab administered either biweekly (77 patients with 500 mg/m^2 every two weeks) or weekly (17 patients with 400 mg/m^2 initial dose followed by 250 mg/m^2 weekly). Treatment continued until unacceptable toxicity or disease progression. Tumor assessments were performed every 6 weeks. Adagrasib discontinuation required cetuximab discontinuation, however patients could continue to receive adagrasib if cetuximab was discontinued [see Dosage and Administration (2.3)]. Six patients continued with adagrasib single agent therapy after discontinuing cetuximab. The length of time these 6 patients received adagrasib alone ranged from 43 days to 3 years. Patient treatment with adagrasib after disease progression continued if a patient was clinically stable and considered to be deriving clinical benefit by the investigator.

The major efficacy outcome measures were confirmed ORR and DOR according to RECIST v1.1 as assessed by BICR.

In the efficacy population, KRAS G12C mutation status was determined by prospective local testing using tumor tissue specimens. Of the 94 patients with KRAS G12C mutation, tissue samples from 79% (74/94) patients were tested retrospectively using the QIAGEN therascreen KRAS RGQ PCR Kit. Of the 74 tissue samples submitted, 81% (60/74) yielded a result with 93% (56/60) positive for KRAS G12C and 7% (4/60) without a KRAS G12C mutation identified.

The baseline demographic and disease characteristics in the efficacy population were: median age 57 years (range: 24 to 75 years), 53% female, 71% White, 14% were Black or African American, 5% Asian, 1.1% American Indian or Alaska Native, 9% reported as other; 51% ECOG PS 0 and 49% ECOG PS 1. Tumor histology was 100% adenocarcinoma and 99% of patients had metastatic disease. Patients received a median of 3 prior systemic therapies (range 1 to 9); 9% received 1 prior line, 36% received 2 prior lines, 31% received 3 prior lines and 25% received 4 or more prior lines. Sites of metastatic disease included lung (71%), liver (64%) and bone (14%).

Efficacy results are summarized in Table 10.

Table 10: Efficacy Results for KRYSTAL-1
Efficacy Parameter | Adagrasib (n = 94)
Objective Response Rate (95% CI) [Assessed by BICR.] | 34 (25, 45)
Complete response rate, % | 0
Partial response rate, % | 34.0
Duration of Response
Median [Estimate using Kaplan-Meier method.] in months (95% CI) | 5.8 (4.2, 7.6)
Patients with duration ≥ 6 months [Observed proportion of patients with duration of response beyond landmark time.] , % | 31
CI = Confidence Interval

16 HOW SUPPLIED/STORAGE AND HANDLING

How Supplied

KRAZATI (adagrasib) tablets, 200 mg, oval shaped, white to off-white, immediate release, film coated tablets with "200" on one side and stylized "M" on the other side.

KRAZATI (adagrasib) tablets are packaged in high-density polyethylene, white opaque, square bottles with desiccant and polypropylene, white, child resistant closures with a tamper-proof heat induction seal.

NDC 80739-812-12: 200 mg, bottle containing 120 tablets.
NDC 80739-812-18: 200 mg, bottle containing 180 tablets.

Storage and Handling

Store tablets at room temperature, 20°C to 25°C (68°F to 77°F). Temperature excursions between 15°C and 30°C (59°F to 86°F) are permitted [see USP Controlled Room Temperature].

17 PATIENT COUNSELING INFORMATION

Advise the patient to read the FDA-approved patient labeling (Patient Information).

Gastrointestinal Adverse Reactions

Advise patients that KRAZATI can cause severe gastrointestinal adverse reactions and to contact their healthcare provider for signs or symptoms of severe or persistent gastrointestinal adverse reactions [see Warnings and Precautions (5.1)].

QTc Interval Prolongation

Advise patients that KRAZATI can cause QTc interval prolongation and to contact their healthcare provider for signs or symptoms of arrhythmias [see Warnings and Precautions (5.2)].

Hepatotoxicity

Advise patients that KRAZATI can cause hepatotoxicity and to immediately contact their healthcare provider for signs or symptoms of liver dysfunction [see Warnings and Precautions (5.3)].

Interstitial Lung Disease (ILD)/Pneumonitis

Advise patients that KRAZATI can cause ILD / pneumonitis and to contact their healthcare provider immediately for new or worsening respiratory symptoms [see Warnings and Precautions (5.4)].

Drug Interactions

Advise patients to inform their healthcare providers of all concomitant medications, including prescription medicines, over-the-counter drugs, vitamins, and herbal products [see Drug Interactions (7.1)].

Missed Dose

If a dose of KRAZATI is missed by greater than 4 hours, resume dosing at the next scheduled time [see Dosage and Administration (2.2)].

Lactation

Advise women not to breastfeed during treatment with KRAZATI and for 1 week after the last dose [see Use in Specific Populations (8.2)].

Infertility

Inform patients that KRAZATI may cause infertility [see Use in Specific Populations (8.3)].

KRAZATI (adagrasib)

Distributed by:
Bristol-Myers Squibb Company
Princeton, NJ 08543 U.S.A.

KRAZATI and the KRAZATI logo are trademarks of Mirati Therapeutics, Inc., a Bristol Myers Squibb company.

PATIENT INFORMATION
KRAZATI® (krah zah tee)
(adagrasib)
Tablets

What is KRAZATI?
KRAZATI is a prescription medicine used in adults:

- alone to treat non-small cell lung cancer (NSCLC)
  - that has spread to other parts of the body or cannot be removed by surgery, and
  - whose tumor has an abnormal KRAS G12C gene, and
  - who have received at least one prior treatment.
- in combination with a medicine called cetuximab to treat colon or rectal cancer (CRC)
  - that has spread to other parts of the body or cannot be removed by surgery, and
  - whose tumor has an abnormal KRAS G12C gene, and
  - who have previously received certain chemotherapy medicines.

Your healthcare provider will perform a test to make sure that KRAZATI is right for you.
It is not known if KRAZATI is safe and effective in children.

Before taking KRAZATI, tell your healthcare provider about all of your medical conditions, including if you:

- have any heart problems, including heart failure and congenital long QT syndrome.
- have liver problems.
- are pregnant or plan to become pregnant. It is not known if KRAZATI can harm your unborn baby.
- are breastfeeding or plan to breastfeed. It is not known if KRAZATI passes into your breastmilk. Do not breastfeed during treatment and for 1 week after your last dose of KRAZATI.

Tell your healthcare provider about all the medicines you take, including prescription and over-the-counter medicines, vitamins, and herbal supplements. KRAZATI can affect the way other medicines work, and other medicines can affect how KRAZATI works.

How should I take KRAZATI?

- Take KRAZATI exactly as your healthcare provider tells you to take it. Do not change your dose or stop taking KRAZATI unless your healthcare provider tells you to.
- Your healthcare provider may change your dose, or temporarily or permanently stop treatment with KRAZATI if you develop certain side effects.
- For colon or rectal cancer, you will also receive cetuximab through a vein in your arm (intravenously) given by your healthcare provider. Your healthcare provider will permanently or temporarily stop your treatment with cetuximab if your treatment with KRAZATI is permanently or temporarily stopped.
- Take your prescribed dose of KRAZATI 2 times each day, at about the same time each day.
- Take KRAZATI either with food or without food.
- Swallow KRAZATI tablets whole. Do not chew, crush or split tablets.
- If you vomit after taking a dose of KRAZATI, do not take an extra dose. Take your next dose at your next scheduled time.
- If you miss a dose of KRAZATI, take the dose as soon as you remember. If it has been more than 4 hours, do not take the dose. Take your next dose of KRAZATI at your next scheduled time. Do not take 2 doses at the same time to make up for a missed dose.

What are possible side effects of KRAZATI?
KRAZATI can cause serious side effects, including:

- Stomach and intestinal (gastrointestinal) problems. Stomach and intestinal side effects including nausea, diarrhea, or vomiting, are common with KRAZATI but can also sometimes be severe. KRAZATI can also cause serious stomach and intestinal side effects such as bleeding, obstruction, inflammation of the colon (colitis), and narrowing (stenosis).
  - Call your healthcare provider if you develop any of the signs or symptoms of stomach or intestinal problems listed above during treatment with KRAZATI.
  - Your healthcare provider may prescribe an antidiarrheal medicine or anti-nausea medicine, or other treatment, as needed.
- Changes in the electrical activity of your heart called QTc prolongation. Certain changes can occur in the electrical activity of your heart during treatment with KRAZATI and can be seen on a test called an electrocardiogram (ECG or EKG). QTc prolongation can increase your risk for irregular heartbeats that can be life-threatening, such as torsades de pointes, and can lead to sudden death.
  - You should not take KRAZATI if you have congenital long QT syndrome or if you currently have QTc prolongation. See "Before taking KRAZATI, tell your healthcare provider about all of your medical conditions, including if you:"
    - Your healthcare provider should monitor the electrical activity of your heart and the levels of body salts in your blood (electrolytes) especially potassium and magnesium before starting and during treatment with KRAZATI if you have heart failure, a slow heart rate, abnormal levels of electrolytes in your blood, or if you take a medicine that can prolong the QT interval of your heartbeat.
    - Tell your healthcare provider if you feel dizzy, lightheaded, or faint, or if you get abnormal heartbeats during treatment with KRAZATI.
- Liver problems. Abnormal liver blood test results are common with KRAZATI and can sometimes be severe. Your healthcare provider should do blood tests before starting and during treatment with KRAZATI to check your liver function. Tell your healthcare provider right away if you develop any signs or symptoms of liver problems, including:

- your skin or the white part of your eyes turns yellow (jaundice)
- dark or "tea-colored" urine
- light-colored stools (bowel movements)
- tiredness or weakness

- nausea or vomiting
- bleeding or bruising
- loss of appetite
- pain, aching or tenderness on the right side of your stomach area (abdomen)

- Lung or breathing problems. KRAZATI may cause inflammation of the lungs that can lead to death. Tell your healthcare provider or get emergency medical help right away if you have new or worsening shortness of breath, cough, or fever.

The most common side effects of KRAZATI when used alone for NSCLC include:

- nausea
- diarrhea
- vomiting
- tiredness
- muscle and bone pain

- kidney problems
- swelling
- decreased appetite
- trouble breathing

The most common side effects of KRAZATI when used in combination with cetuximab for CRC include:

- skin rash
- nausea
- diarrhea
- vomiting
- tiredness
- muscle and bone pain
- headache
- dry skin

- stomach pain
- decreased appetite
- swelling
- low red blood cell count
- cough
- dizziness
- constipation
- nerve damage in the arms and legs

Certain abnormal blood test results are common during treatment with KRAZATI, when used alone or in combination with cetuximab. Your healthcare provider will monitor you for abnormal blood tests and treat you if needed.

KRAZATI may cause fertility problems in males and females, which may affect your ability to have children. Talk to your healthcare provider if this is a concern for you.
These are not all of the possible side effects of KRAZATI.
Call your doctor for medical advice about side effects. You may report side effects to FDA at 1-800-FDA-1088.

How should I store KRAZATI?

- Store KRAZATI at room temperature between 68°F to 77°F (20°C to 25°C).
- KRAZATI comes in a child-resistant container.
- KRAZATI comes with a desiccant (drying agent) in the container to keep the medicine dry. Do not remove the desiccant from the container after opening. Do not eat or swallow the desiccant.

Keep KRAZATI and all medicines out of the reach of children.

General information about the safe and effective use of KRAZATI.
Medicines are sometimes prescribed for purposes other than those listed in a Patient Information leaflet. Do not use KRAZATI for a condition for which it was not prescribed. Do not give KRAZATI to other people, even if they have the same symptoms that you have. It may harm them. You can ask your pharmacist or healthcare provider for information about KRAZATI that is written for health professionals.

What are the ingredients in KRAZATI?
Active ingredient: adagrasib
Inactive ingredients: colloidal silicon dioxide, crospovidone, magnesium stearate (vegetable sourced), mannitol, and microcrystalline cellulose. The tablet film coating contains hypromellose, maltodextrin, medium chain triglycerides (vegetable sourced), polydextrose, talc, and titanium dioxide.
Distributed by: Bristol-Myers Squibb Company, Princeton, NJ 08543 U.S.A.
KRAZATI and the KRAZATI logo are trademarks of Mirati Therapeutics, Inc., a Bristol Myers Squibb company.
For more information, go to www.KRAZATI.com or call 1-866-4-KRAZATI (1-866-457-2928).

This Patient Information has been approved by the U.S. Food and Drug Administration. Revised: 07/2024

PRINCIPAL DISPLAY PANEL - 180 Tablet Bottle Carton

NDC 80739-812-18

Rx Only

KRAZATI®
(adagrasib tablets)

200 mg

180 tablets

Bristol Myers Squibb®